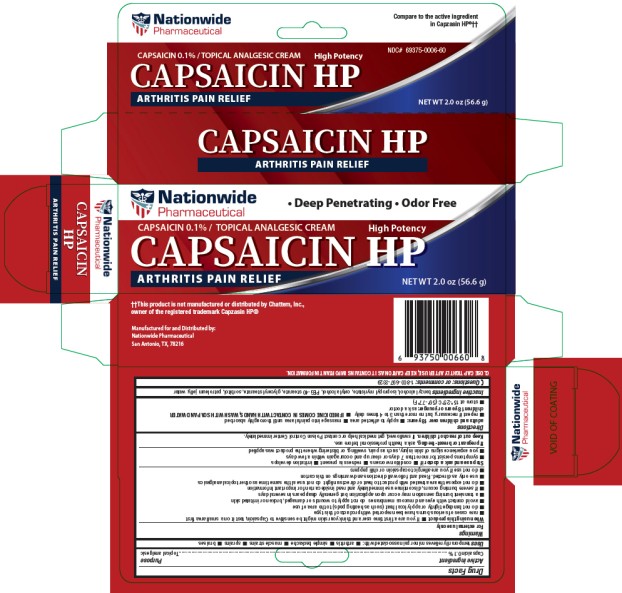 DRUG LABEL: Capsaicin HP Arthritis Pain Relief
NDC: 69375-006 | Form: CREAM
Manufacturer: Nationwide Pharmaceutical LLC
Category: otc | Type: HUMAN OTC DRUG LABEL
Date: 20250609

ACTIVE INGREDIENTS: CAPSAICIN 0.1 g/100 g
INACTIVE INGREDIENTS: BENZYL ALCOHOL; ISOPROPYL MYRISTATE; CETYL ALCOHOL; PEG-40 STEARATE; GLYCERYL MONOSTEARATE; SORBITOL; PETROLATUM; WATER

Capsaicin Cream

Drug Facts

Active ingredient

Capsaicin 0.1%

Purpose

Topical analgesic

Uses

temporarily relieves minor pain associated with:

- arthritis
- simple backache
- muscle strains
- sprains
- bruises

Warnings

For external use only

When using this product

- If you are a first time user and think your skin might be sensitive to Capsaicin, test it on a small area first
- rare cases of serious burns have been reported with products of this type
- do not bandage tightly or apply local heat (such as heating pads) to the area of use
- avoid contact with eyes and mucous membranes do not apply to wounds or damaged, broken or irritated skln
- a transient burning sensation may occur upon application but generally disappears in several days
- if severe burning occurs, discontinue use immediately and read inside carton for important Information
- do not expose the area treated with product to heat or direct sunlight do not use al the same time as other topical analgesics
- use only as directed. Read and follow all directions and warnings on this carton
- do not use if you are allergic to capsaicin or chili peppers

Stop use and ask a doctor if

- condition worsens
- redness is present
- irritation develops
- symptoms persist for more than 7 days or clear up and occur again within a few days
- you experience signs of skin injury, such as pain, swelling, or blistering where the product was applied

If pregnant or breast-feeding,

ask a health professional before use.

Keep out of reach of children.

If swallowed, get medical help or contact Poison Control Center immediately.

Directions

adults and children over 18 years:

- apply to affected area
- massage into painful area until thoroughly absorbed
- repeat if necessary, but no more than 3 to 4 times daily
- IF MEDICINE COMES IN CONTACT WITH HANDS, WASH WITH SOAP AND WATER

children 18 years or younger: ask a doctor

- store at 15°-25°C (59°-77°F)

Inactive ingredients

benzyl alcohol, isopropyl myristate, cetyl alcohol, PEG-40 stearate, glyceryl stearate, sorbitol, petroleum jelly, water

Questions: or comments

1-800-697-3329

Manufactured for and Distributed by:
Nationwide Pharmaceutical
San Antonio, TX, 78216

PRINCIPAL DISPLAY PANEL - 56.6 g Tube Carton

Nationwide
Pharmaceutical

• Deep Penetrating • Odor Free

NDC# 69375-0006-60

CAPSAICIN HP
High Potency

CAPSAICIN 0.1% / TOPICAL ANALGESIC CREAM

ARTHRITIS PAIN RELIEF

Compare to the
active ingredient
in Capzasin HP®††

NET WT 2.0 oz (56.6 g)